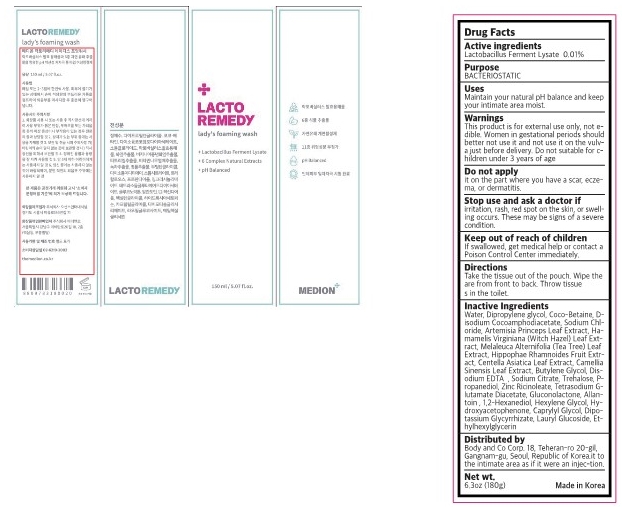 DRUG LABEL: LACTO REMEDY Ladys foaming wash
NDC: 83490-303 | Form: LIQUID
Manufacturer: 2359 US INC
Category: otc | Type: HUMAN OTC DRUG LABEL
Date: 20230524

ACTIVE INGREDIENTS: LIMOSILACTOBACILLUS FERMENTUM 0.0176 g/100 g
INACTIVE INGREDIENTS: COCO-BETAINE; HAMAMELIS VIRGINIANA LEAF; CENTELLA ASIATICA LEAF; WATER; SODIUM CITRATE; PROPANEDIOL; GLUCONOLACTONE; HEXYLENE GLYCOL; HYDROXYACETOPHENONE; CAPRYLYL GLYCOL; GLYCYRRHIZINATE DIPOTASSIUM; DIPROPYLENE GLYCOL; DISODIUM COCOAMPHODIACETATE; SODIUM CHLORIDE; ARTEMISIA PRINCEPS LEAF; MELALEUCA ALTERNIFOLIA LEAF; HIPPOPHAE RHAMNOIDES FRUIT; GREEN TEA LEAF; BUTYLENE GLYCOL; EDETATE DISODIUM ANHYDROUS; ZINC RICINOLEATE; TETRASODIUM GLUTAMATE DIACETATE; ALLANTOIN; 1,2-HEXANEDIOL; ETHYLHEXYLGLYCERIN; LAURYL GLUCOSIDE; TREHALOSE

LACTO REMEDY lady's foaming wash 83490-303

active ingredient

Lactobacillus Ferment Lysate 0.01%

purpose

BACTERIOSTATIC

use

Maintain your natural pH balance and keep your intimate area moist.

warnings

Do not suitable for c- hildren under 3 years of age

warnings

This product is for external use only, not e- dible. Women in gestational periods should better not use it and not use it on the vulv- a just before delivery.

warnings

Stop use and ask a doctor if irritation, rash, red spot on the skin, or swelling occurs. These may be signs of a severe
condition.

warnings

Keep out of reach of children
If swallowed, get medical help or contact a Poison Control Center immediately.

Directions

Take the tissue out of the pouch. Wipe the are from front to back. Throw tissues in the toilet.

inactive ingredient

Water, Dipropylene glycol, Coco-Betaine, D- isodium Cocoamphodiacetate, Sodium Chl- oride, Artemisia Princeps Leaf Extract, Ha- mamelis Virginiana (Witch Hazel) Leaf Ext- ract, Melaleuca Alternifolia (Tea Tree) Leaf Extract, Hippophae Rhamnoides Fruit Extr- act, Centella Asiatica Leaf Extract, Camellia Sinensis Leaf Extract, Butylene Glycol, Dis- odium EDTA , Sodium Citrate, Trehalose, P- ropanediol, Zinc Ricinoleate, Tetrasodium G- lutamate Diacetate, Gluconolactone, Allan- toin , 1,2-Hexanediol, Hexylene Glycol, Hy- droxyacetophenone, Caprylyl Glycol, Dipo- tassium Glycyrrhizate, Lauryl Glucoside, Et- hylhexylglycerin

WARNINGS

This product is for external use only, not edible.

label

LACTO REMEDY lady's foaming wash 82892-303